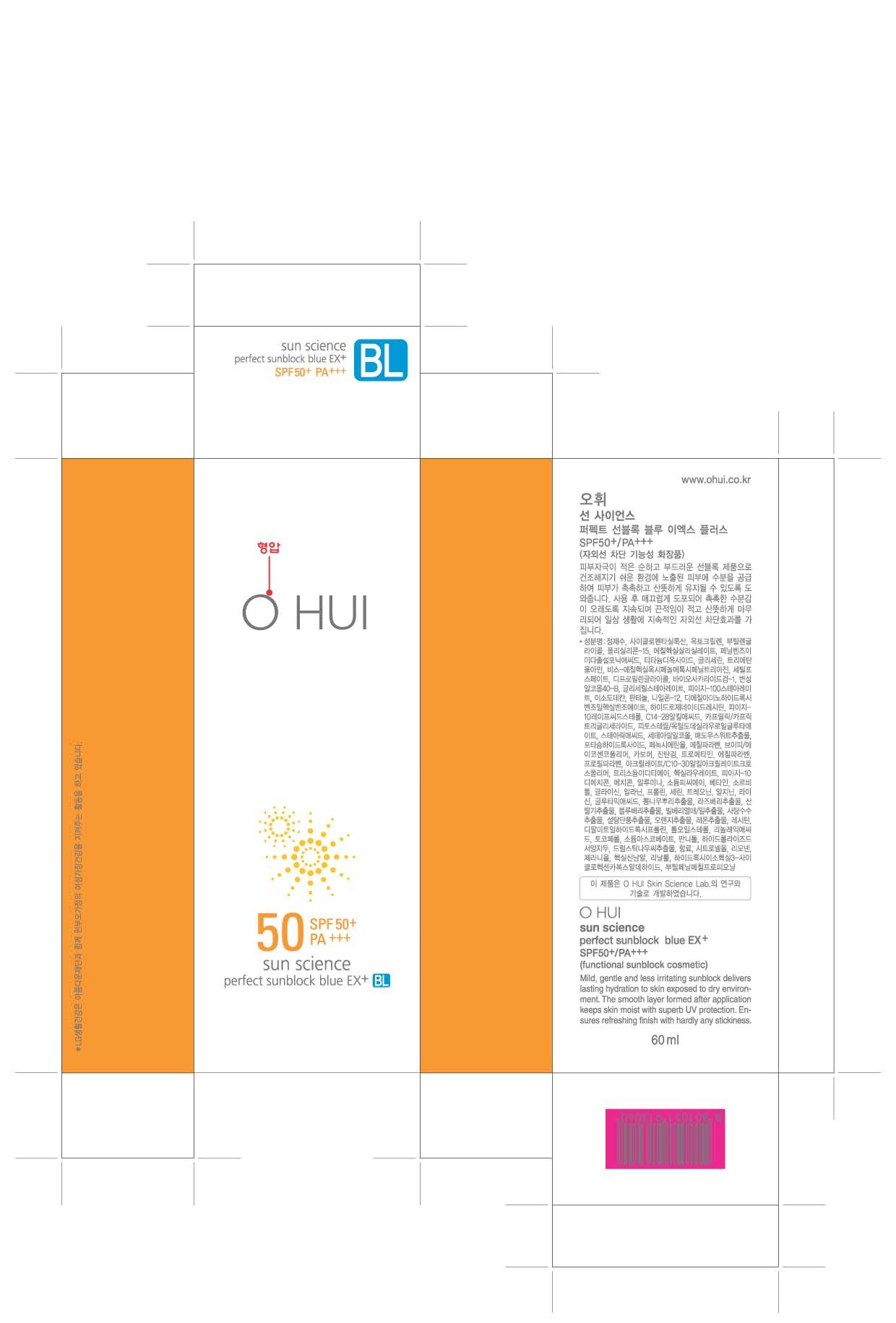 DRUG LABEL: OHUI SUN SCIENCE Perfect Sunblock Blue EX plus
NDC: 53208-539 | Form: CREAM
Manufacturer: LG Household and Healthcare, Inc.
Category: otc | Type: HUMAN OTC DRUG LABEL
Date: 20110803

ACTIVE INGREDIENTS: TITANIUM DIOXIDE 9 mL/100 mL; POLYSILICONE-15 5 mL/100 mL; OCTISALATE 4.8 mL/100 mL; ENSULIZOLE 3.9 mL/100 mL; BEMOTRIZINOL 2 mL/100 mL
INACTIVE INGREDIENTS: WATER; CYCLOMETHICONE 5; BUTYLENE GLYCOL; GLYCERIN; BIOSACCHARIDE GUM-1; TROLAMINE; CETYL PHOSPHATE; DIPROPYLENE GLYCOL; ISODODECANE; PANTHENOL; STEARIC ACID; CETOSTEARYL ALCOHOL; GLYCERYL MONOSTEARATE; POTASSIUM HYDROXIDE; PHENOXYETHANOL; METHYLPARABEN; XANTHAN GUM; ETHYLPARABEN; PROPYLPARABEN; EDETATE TRISODIUM; MORINGA OLEIFERA SEED

Drug Facts

ACTIVE INGREDIENT

TITANIUM DIOXIDE 9%

OCTOCRYLENE 7%

POLYSILICONE-15 5%

OCTISALATE 4.8%

ENSULIZOLE 3.9%

BEMOTRIZINOL 2%

WARNINGS AND PRECAUTIONS

For external use only.

KEEP OUT OF REACH OF CHILDREN

If swallowed, get medical help or contact a Poison Control Center right away.

Stop use if a rash or irritation develops and lasts.

WHEN USING

Keep out of eyes. Rinse with water to remove.

PACKAGE LABEL

OHUI SUN SCIENCE PERFECT SUNBLOCK Blue EX